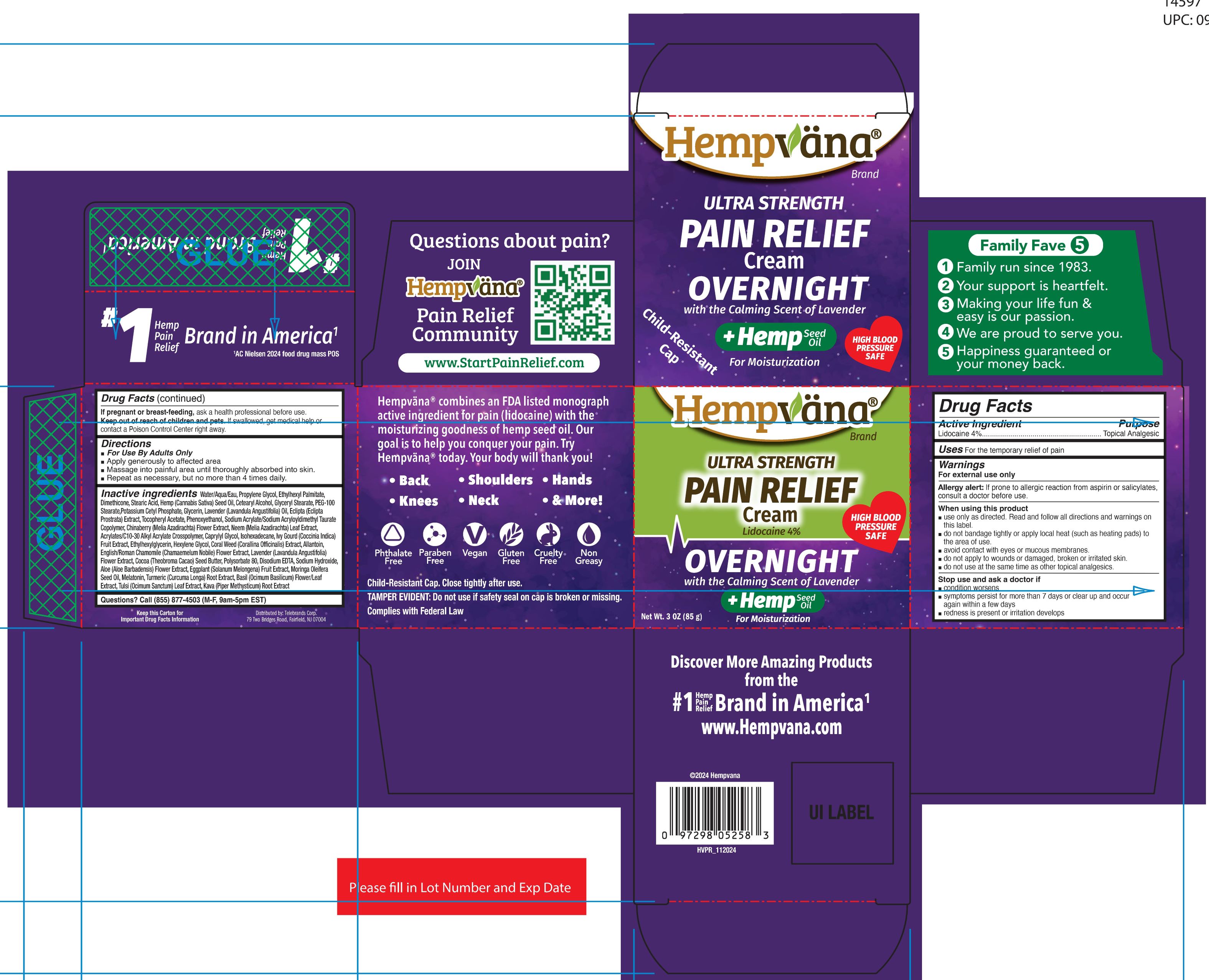 DRUG LABEL: Hempvana Ultra Strength Pain Relief - Overnight
NDC: 73287-029 | Form: CREAM
Manufacturer: Telebrands Corp
Category: otc | Type: HUMAN OTC DRUG LABEL
Date: 20241202

ACTIVE INGREDIENTS: LIDOCAINE 4 g/100 g
INACTIVE INGREDIENTS: OCIMUM BASILICUM (BASIL) FLOWER/LEAF EXTRACT; ECLIPTA PROSTRATA WHOLE; MELIA AZEDARACH WHOLE; ALOE BARBADENSIS FLOWER EXTRACT; CURCUMA LONGA (TURMERIC) ROOT EXTRACT; OCIMUM TENUIFLORUM WHOLE; PEG-100 STEARATE; GLYCERYL MONOSTEARATE; CANNABIS SATIVA SEED OIL; SODIUM HYDROXIDE; STEARIC ACID; LAVANDULA ANGUSTIFOLIA FLOWER; ETHYLHEXYL PALMITATE; WATER; CETOSTEARYL ALCOHOL; GLYCERIN; ISOHEXADECANE; HEXYLENE GLYCOL; ACRYLATES/C10-30 ALKYL ACRYLATE CROSSPOLYMER (60000 MPA.S); PHENOXYETHANOL; DIMETHICONE; LAVENDER OIL; ALLANTOIN; PIPER METHYSTICUM ROOT; POTASSIUM CETYL PHOSPHATE; ALPHA-TOCOPHEROL ACETATE; COCOA BUTTER; PROPYLENE GLYCOL; CHAMAEMELUM NOBILE FLOWER; MELATONIN; SODIUM ACRYLATE/SODIUM ACRYLOYLDIMETHYLTAURATE COPOLYMER (4000000 MW); CAPRYLYL GLYCOL; ETHYLHEXYLGLYCERIN; POLYSORBATE 80; EDETATE DISODIUM ANHYDROUS; CORALLINA OFFICINALIS EXTRACT; MELIA AZADIRACHTA LEAF; COCCINIA INDICA FRUIT EXTRACT; MORINGA OLEIFERA SEED OIL; SOLANUM MELONGENA WHOLE

Active Ingredient

Lidocaine 4%

Purpose

Lidocaine 4%...... Topical Analgesic

Uses

For the temporary relief of pain

Warnings

For external use only

Allergy alert:If prone to allergic reaction from aspirin or salicylates, consult a doctor before use.

When using this product
■ use only as directed. Read and follow all directions and warnings on this label.
■ do not bandage tightly or apply local heat (such as heating pads) to the area
of use.
■ avoid contact with eyes or mucous membranes.
■ do not apply to wounds or damaged, broken or irritated skin.
■ do not use at the same time as other topical analgesics.
■ do not use in large quantities, particularly over raw surfaces or blistered areas.

Stop use and ask a doctor if
■ condition worsens
■ symptoms persist for more than 7 days or clear up and occur
again within a few days
■ redness is present or irritation develops

PREGNANCY OR BREAST FEEDING

If pregnant or breast-feeding, ask a health professional before use.

Keep out of reach of children and pets.If swallowed, get medical help or contact a Poison Control Center right away.

Directions

■ For Use By Adults Only
■ Apply generously to affected area
■ Massage into painful area until thoroughly absorbed into skin.
■ Repeat as necessary, but no more than 4 times daily.

Inactive Ingredients

Water/Aqua/Eau, Propylene Glycol, Ethylhexyl Palmitate,Dimethicone, Stearic Acid, Hemp (Cannabis Sativa) Seed Oil, Cetearyl Alcohol, Glyceryl Stearate, PEG-100Stearate,Potassium Cetyl Phosphate, Glycerin, Lavender (Lavandula Angustifolia) Oil, Eclipta (EcliptaProstrata) Extract, Tocopheryl Acetate, Phenoxyethanol, Sodium Acrylate/Sodium Acryloyldimethyl TaurateCopolymer, Chinaberry (Melia Azadirachta) Flower Extract, Neem (Melia Azadirachta) Leaf Extract,Acrylates/C10-30 Alkyl Acrylate Crosspolymer, Caprylyl Glycol, Isohexadecane, Ivy Gourd (Coccinia Indica)Fruit Extract, Ethylhexylglycerin, Hexylene Glycol, Coral Weed (Corallina Officinalis) Extract, Allantoin,English/Roman Chamomile (Chamaemelum Nobile) Flower Extract, Lavender (Lavandula Angustifolia)Flower Extract, Cocoa (Theobroma Cacao) Seed Butter, Polysorbate 80, Disodium EDTA, Sodium Hydroxide,Aloe (Aloe Barbadensis) Flower Extract, Eggplant (Solanum Melongena) Fruit Extract, Moringa OleiferaSeed Oil, Melatonin, Turmeric (Curcuma Longa) Root Extract, Basil (Ocimum Basilicum) Flower/LeafExtract, Tulsi (Ocimum Sanctum) Leaf Extract, Kava (Piper Methysticum) Root Extract

Questions

Call (855) 877-4503 (M-F, 9am-5pm EST)

PACKAGE LABEL

Hempvana

Ultra Strength

Pain Relief

Cream

Lidocaine 4%

Overnight

Calming Scent of Lavender

+ Hemp Seed Oil

For Moisturization

Net Wt. 3oz (85 g)